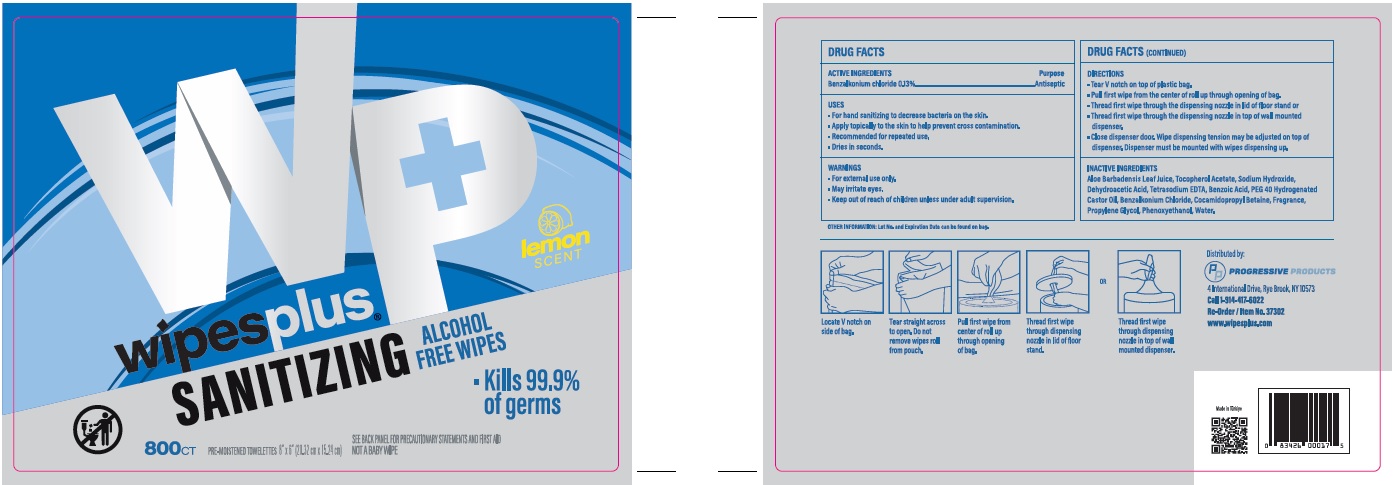 DRUG LABEL: Benzalkonium Chloride
NDC: 67151-323 | Form: CLOTH
Manufacturer: Progressive
Category: otc | Type: HUMAN OTC DRUG LABEL
Date: 20221014

ACTIVE INGREDIENTS: BENZALKONIUM CHLORIDE 0.0043524 g/1 1
INACTIVE INGREDIENTS: ALOE VERA WHOLE; DEHYDROACETIC ACID; WATER; COCAMIDOPROPYL BETAINE; EDETATE SODIUM; PHENOXYETHANOL; HYDROGENATED CASTOR OIL; BENZOIC ACID; SODIUM HYDROXIDE; ALPHA-TOCOPHEROL ACETATE

Wipe Plus 800ct

Active Ingredient

Benzalkonium Chloride 0.13%

Purpose

Antiseptic

Uses

- For hand sanitizing to decrease bacteria on the skin.
- Apply topically to the skin to help prevent cross contamination.
- Recommended for repeated use.
- Dries in seconds.

Warnings

For external use only.

May irritate eyes.

Keep out of reach of children unless under adult supervision

Directions

- Tear V notch on top of plastic bag.
- Pull first wipe from the center of roll through opening of bag.
- Thread first wipe through the dispensing nozzle in lid of floor stand or
- Thread first wipe through the dispensing nozzle in top of wall mounted dispenser.
- Close dispenser door. Wipe dispensing tension may be adjusted on top of dispenser. Dispenser must be mounted with wipes disepensing up.

Inactive Ingredients

Aloe Barbadensis Leaf Juice, Tocopherol Acetate, Sodium Hydroxide, Dehydroacetic Acid, Tetrasodium EDTA, Benzoic Acid, PEG 40 Hydrogenated Castor Oil, Benzalkonium Chloride, Cocamidapropyl Betaine, Fragrance, Propylene Glycol, Phenoxyethanol, Water.

Principal Display Panel

wipes plus

SANITIZING ALCOHOL FREE WIPES

- Kills 99.9% of germs

800 CT